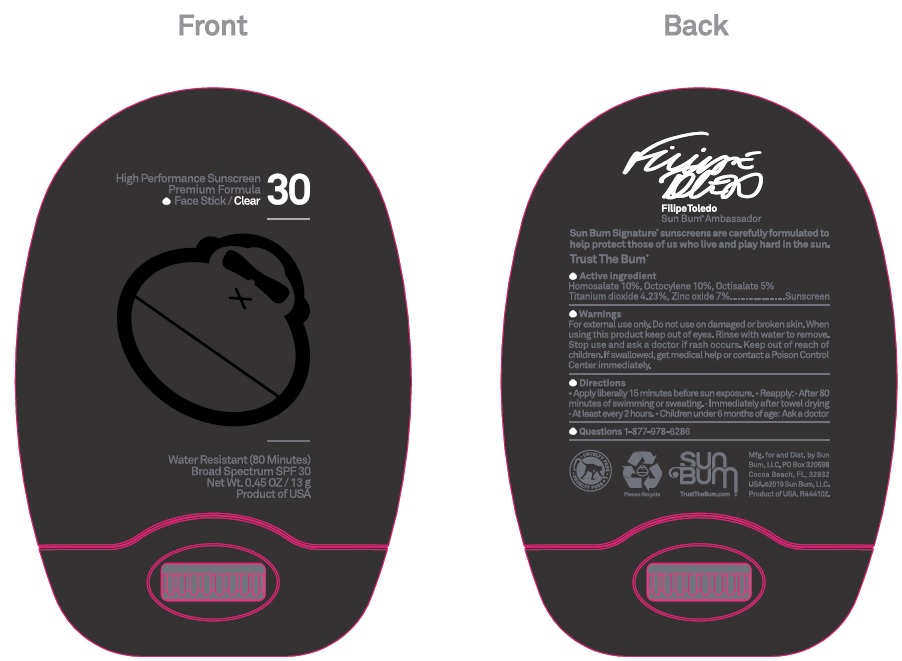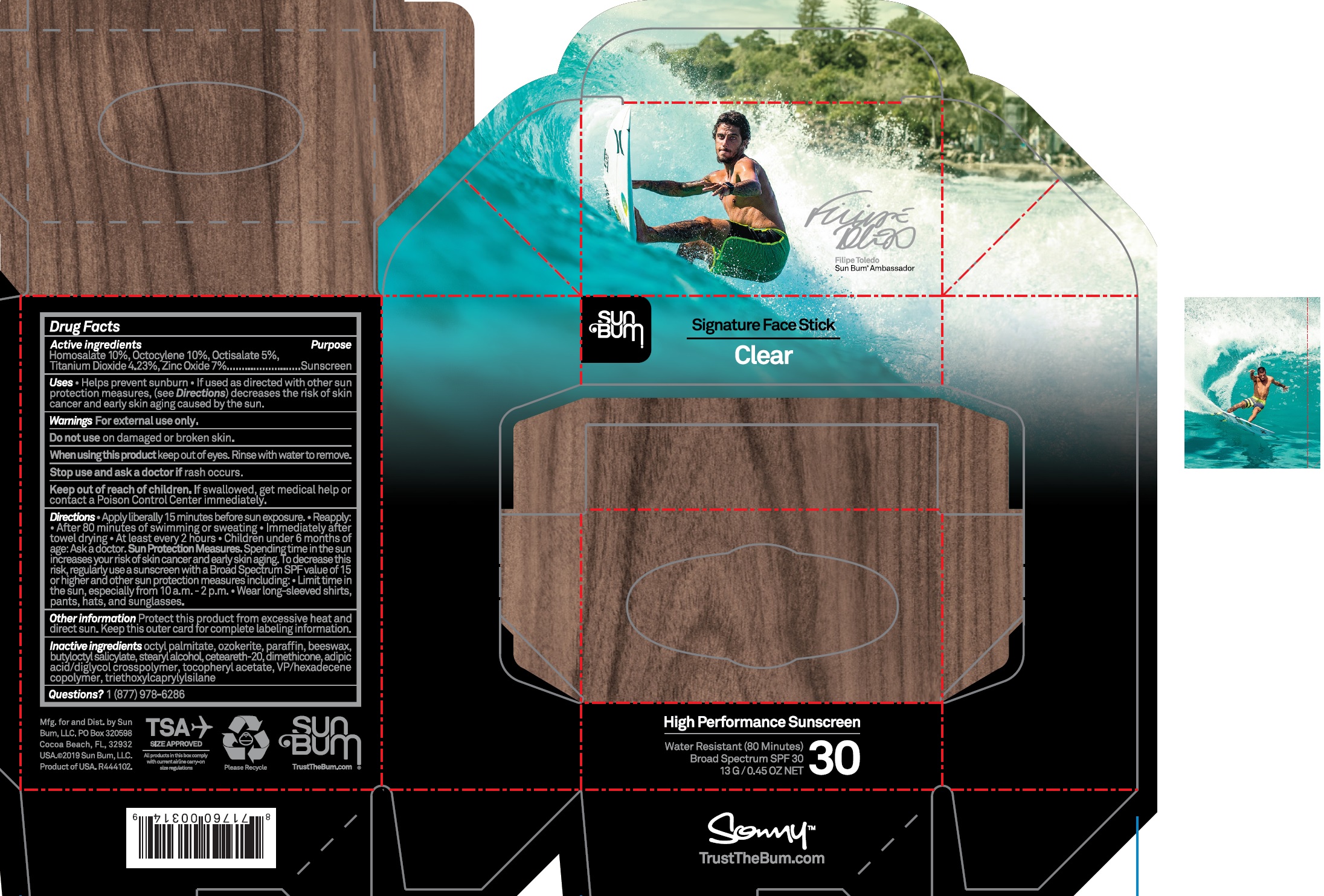 DRUG LABEL: Signature SPF 50 Clear Face
NDC: 69039-610 | Form: STICK
Manufacturer: Sun Bum LLC
Category: otc | Type: HUMAN OTC DRUG LABEL
Date: 20220322

ACTIVE INGREDIENTS: HOMOSALATE 100 mg/1 g; OCTOCRYLENE 100 mg/1 g; OCTISALATE 50 mg/1 g; TITANIUM DIOXIDE 42.3 mg/1 g; ZINC OXIDE 70 mg/1 g
INACTIVE INGREDIENTS: ETHYLHEXYL PALMITATE; CERESIN; PARAFFIN; YELLOW WAX; BUTYLOCTYL SALICYLATE; STEARYL ALCOHOL; POLYOXYL 20 CETOSTEARYL ETHER; DIMETHICONE; ADIPIC ACID/DIGLYCOL CROSSPOLYMER (20000 MPA.S); .ALPHA.-TOCOPHEROL ACETATE; VINYLPYRROLIDONE/HEXADECENE COPOLYMER; TRIETHOXYCAPRYLYLSILANE

Signature SPF 50 Clear Face Stick

Active ingredients

Homosalate 10%, Octocrylene 10%, Octisalate 5%, Titanium Dioxide4.23%, Zinc Oxide 7%

Purpose

Sunscreen

Uses

- Helps prevent sunburn
- If used as directed with other sun protection measures, (see Directions) decreases the risk of skin cancer and early skin aging caused by the sun

Warnings

For external use only

Do not use

on damaged or broken skin.

When using this product

keep out of eyes. Rinse with water to remove.

Stop use and ask a doctor

if rash occurs

Keep out of reach of children.

If swallowed, get medical help or contact a Poison Control Center immediately.

Directions

- Apply liberally 15 minutes before sun exposure
- Reapply: After 80 minutes of swimming or sweating
- Immediately after towel drying
- At least every 2 hours
- Children under 6 months of age: Ask a doctor

Sun Protection Measures. Spending time in the sun increases your risk of skin cancer and early skin aging. To decrease this risk, regularly use a sunscreen with a Broad Spectrum SPF value of 15 or higher and other sun protection measures including:

- Limit time in the sun, especially from 10 a.m.-2 p.m.
- Wear long-sleeved shirts, pants, hats and sunglasses

Other information

Protect this product from excessive heat and direct sun. Keep this outer card for complete labeling information.

Inactive ingredients

octyl palmitate, ozokerite, paraffin, beeswax, butyloctyl salicylate, stearyl alcohol, ceteareth-20, dimethicone, adipic acid/diglycol crosspolymer, tocopheryl acetate, VP/hexadecene copolymer, triethoxycaprylylsilane

Questions?

1 (877) 978-6286